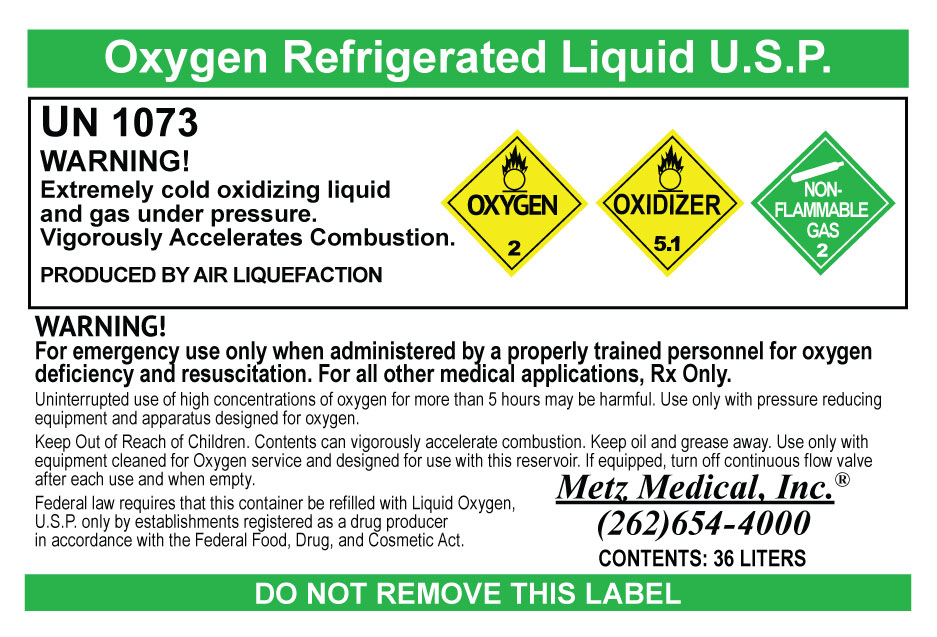 DRUG LABEL: Liquid Oxygen
NDC: 66767-998 | Form: GAS
Manufacturer: Metz Medical, Inc
Category: prescription | Type: HUMAN PRESCRIPTION DRUG LABEL
Date: 20151203

ACTIVE INGREDIENTS: OXYGEN 99 L/100 L

Liquid Oxygen